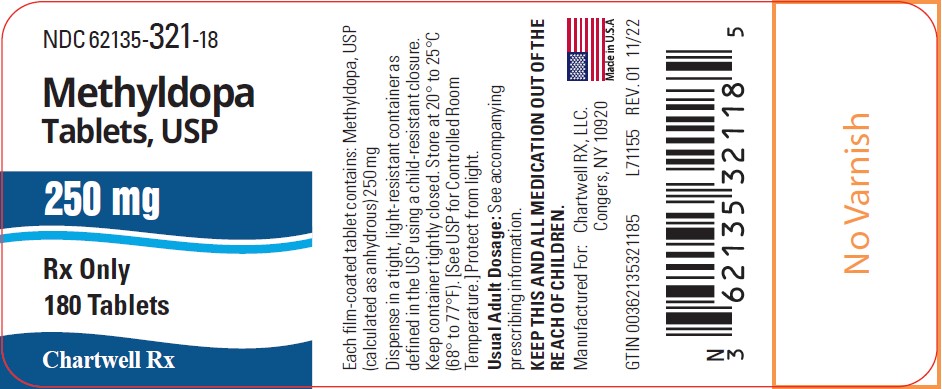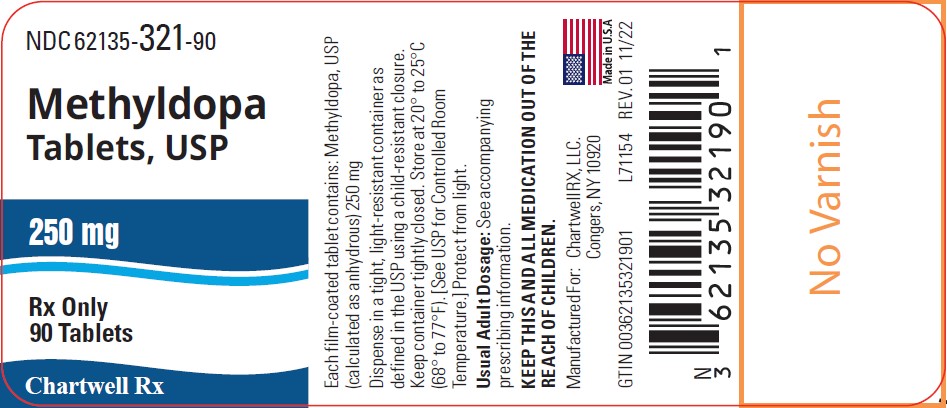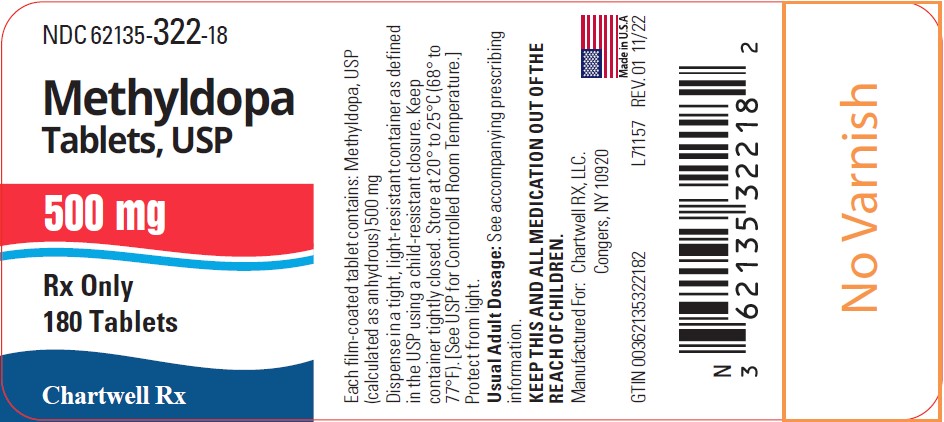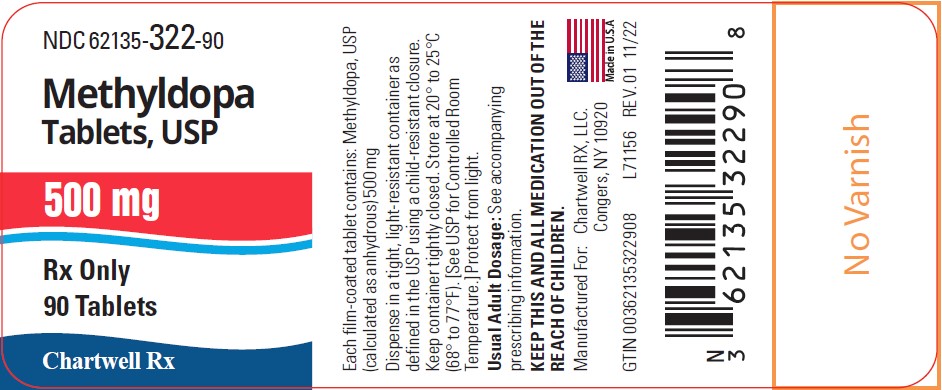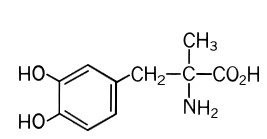 DRUG LABEL: Methyldopa
NDC: 62135-321 | Form: TABLET, FILM COATED
Manufacturer: Chartwell RX, LLC
Category: prescription | Type: HUMAN PRESCRIPTION DRUG LABEL
Date: 20250326

ACTIVE INGREDIENTS: METHYLDOPA 250 mg/1 1
INACTIVE INGREDIENTS: MICROCRYSTALLINE CELLULOSE; ETHYLCELLULOSE, UNSPECIFIED; MAGNESIUM STEARATE; POLYETHYLENE GLYCOL, UNSPECIFIED; LACTOSE MONOHYDRATE; HYPROMELLOSE, UNSPECIFIED; ANHYDROUS CITRIC ACID; STARCH, CORN; SILICON DIOXIDE

Methyldopa Tablets, USP

DESCRIPTION

Methyldopa is an antihypertensive drug.

Methyldopa, the L-isomer of alpha-methyldopa, is levo-3-(3,4-dihydroxyphenyl)-2-methylalanine. Its empirical formula is C10H13NO4, with a molecular weight of 211.22, and its structural formula is:

Methyldopa is a white to yellowish white, odorless fine powder, and is soluble in water.
Methyldopa Tablets, USP is supplied as tablets, for oral use, in two strengths: 250 mg and 500 mg of methyldopa per tablet. Inactive ingredients in the tablets are: lactose monohydrate, hypromellose , citric acid, corn starch, colloidal silicon dioxide, microcrystalline cellulose, ethyl cellulose, magnesium stearate, and polyethylene glycol.

CLINICAL PHARMACOLOGY

Methyldopa is an aromatic-amino-acid decarboxylase inhibitor in animals and in man. Although the mechanism of action has yet to be conclusively demonstrated, the antihypertensive effect of methyldopa probably is due to its metabolism to alpha-methylnorepinephrine, which then lowers arterial pressure by stimulation of central inhibitory alpha-adrenergic receptors, false neurotransmission, and/or reduction of plasma renin activity. Methyldopa has been shown to cause a net reduction in the tissue concentration of serotonin, dopamine, norepinephrine, and epinephrine.

Only methyldopa, the L-isomer of alpha-methyldopa, has the ability to inhibit dopa decarboxylase and to deplete animal tissues of norepinephrine. In man the antihypertensive activity appears to be due solely to the L-isomer. About twice the dose of the racemate (DL-alpha-methyldopa) is required for equal antihypertensive effect.

Methyldopa has no direct effect on cardiac function and usually does not reduce glomerular filtration rate, renal blood flow, or filtration fraction. Cardiac output usually is maintained without cardiac acceleration. In some patients the heart rate is slowed.

Normal or elevated plasma renin activity may decrease in the course of methyldopa therapy.

Methyldopa reduces both supine and standing blood pressure. Methyldopa usually produces highly effective lowering of the supine pressure with infrequent symptomatic postural hypotension. Exercise hypotension and diurnal blood pressure variations rarely occur.

Pharmacokinetics and Metabolism

The maximum decrease in blood pressure occurs four to six hours after oral dosage. Once an effective dosage level is attained, a smooth blood pressure response occurs in most patients in 12 to 24 hours. After withdrawal, blood pressure usually returns to pretreatment levels within 24-48 hours.

Methyldopa is extensively metabolized. The known urinary metabolites are: α-methyldopa mono-0-sulfate; 3-0-methyl-α-methyldopa; 3,4-dihydroxyphenylacetone; α-methyldopamine; 3-0-methyl-α-methyldopamine and their conjugates.

Approximately 70% of the drug which is absorbed is excreted in the urine as methyldopa and its mono-0-sulfate conjugate. The renal clearance is about 130 mL/min in normal subjects and is diminished in renal insufficiency. The plasma half-life of methyldopa is 105 minutes. After oral doses, excretion is essentially complete in 36 hours.

Methyldopa crosses the placental barrier, appears in cord blood, and appears in breast milk.

INDICATION AND USAGE

Hypertension.

CONTRAINDICATIONS

Methyldopa is contraindicated in patients:

— with active hepatic disease, such as acute hepatitis and active cirrhosis

— with liver disorders previously associated with methyldopa therapy (see WARNINGS)

— with hypersensitivity to any component of these products.

— on therapy with monoamine oxidase (MAO) inhibitors.

WARNINGS

It is important to recognize that a positive Coombs test, hemolytic anemia, and liver disorders may occur with methyldopa therapy. The rare occurrences of hemolytic anemia or liver disorders could lead to potentially fatal complications unless properly recognized and managed. Read this section carefully to understand these reactions.

With prolonged methyldopa therapy, 10 to 20 percent of patients develop a positive direct Coombs test which usually occurs between 6 and 12 months of methyldopa therapy. Lowest incidence is at daily dosage of 1 g or less. This on rare occasions may be associated with hemolytic anemia, which could lead to potentially fatal complications. One cannot predict which patients with a positive direct Coombs test may develop hemolytic anemia.

Prior existence or development of a positive direct Coombs test is not in itself a contraindication to use of methyldopa. If a positive Coombs test develops during methyldopa therapy, the physician should determine whether hemolytic anemia exists and whether the positive Coombs test may be a problem. For example, in addition to a positive direct Coombs test there is less often a positive indirect Coombs test which may interfere with cross matching of blood.

Before treatment is started, it is desirable to do a blood count (hematocrit, hemoglobin, or red cell count) for a baseline or to establish whether there is anemia. Periodic blood counts should be done during therapy to detect hemolytic anemia. It may be useful to do a direct Coombs test before therapy and at 6 and 12 months after the start of therapy.

If Coombs-positive hemolytic anemia occurs, the cause may be methyldopa and the drug should be discontinued. Usually the anemia remits promptly. If not, corticosteroids may be given and other causes of anemia should be considered. If the hemolytic anemia is related to methyldopa, the drug should not be reinstituted.

When methyldopa causes Coombs positivity alone or with hemolytic anemia, the red cell is usually coated with gamma globulin of the IgG (gamma G) class only. The positive Coombs test may not revert to normal until weeks to months after methyldopa is stopped.

Should the need for transfusion arise in a patient receiving methyldopa, both a direct and an indirect Coombs test should be performed. In the absence of hemolytic anemia, usually only the direct Coombs test will be positive. A positive direct Coombs test alone will not interfere with typing or cross matching. If the indirect Coombs test is also positive, problems may arise in the major cross match and the assistance of a hematologist or transfusion expert will be needed.

Occasionally, fever has occurred within the first 3 weeks of methyldopa therapy, associated in some cases with eosinophilia or abnormalities in one or more liver function tests, such as serum alkaline phosphatase, serum transaminases (SGOT, SGPT), bilirubin, and prothrombin time. Jaundice, with or without fever, may occur with onset usually within the first 2 to 3 months of therapy. In some patients the findings are consistent with those of cholestasis. In others the findings are consistent with hepatitis and hepatocellular injury.

Rarely, fatal hepatic necrosis has been reported after use of methyldopa. These hepatic changes may represent hypersensitivity reactions. Periodic determinations of hepatic function should be done particularly during the first 6 to 12 weeks of therapy or whenever an unexplained fever occurs. If fever, abnormalities in liver function tests, or jaundice appear, stop therapy with methyldopa. If caused by methyldopa, the temperature and abnormalities in liver function characteristically have reverted to normal when the drug was discontinued. Methyldopa should not be reinstituted in such patients.

Rarely, a reversible reduction of the white blood cell count with a primary effect on the granulocytes has been seen. The granulocyte count returned promptly to normal on discontinuance of the drug. Rare cases of granulocytopenia have been reported. In each instance, upon stopping the drug, the white cell count returned to normal. Reversible thrombocytopenia has occurred rarely.

PRECAUTIONS

General

Methyldopa should be used with caution in patients with a history of previous liver disease or dysfunction (see WARNINGS).

Some patients taking methyldopa experience clinical edema or weight gain which may be controlled by use of a diuretic. Methyldopa should not be continued if edema progresses or signs of heart failure appear.

Hypertension has recurred occasionally after dialysis in patients given methyldopa because the drug is removed by this procedure.

Rarely involuntary choreoathetotic movements have been observed during therapy with methyldopa in patients with severe bilateral cerebrovascular disease. Should these movements occur, stop therapy.

Laboratory Tests

Blood count, Coombs test, and liver function tests are recommended before initiating therapy and at periodic intervals (see WARNINGS).

Drug Interactions

When methyldopa is used with other antihypertensive drugs, potentiation of antihypertensive effect may occur. Patients should be followed carefully to detect side reactions or unusual manifestations of drug idiosyncrasy.

Patients may require reduced doses of anesthetics when on methyldopa. If hypotension does occur during anesthesia, it usually can be controlled by vasopressors. The adrenergic receptors remain sensitive during treatment with methyldopa.

When methyldopa and lithium are given concomitantly the patient should be carefully monitored for symptoms of lithium toxicity. Read the circular for lithium preparations.

Several studies demonstrate a decrease in the bioavailability of methyldopa when it is ingested with ferrous sulfate or ferrous gluconate. This may adversely affect blood pressure control in patients treated with methyldopa. Coadministration of methyldopa with ferrous sulfate or ferrous gluconate is not recommended.

Monoamine oxidase (MAO) inhibitors: see CONTRAINDICATIONS.

Drug/Laboratory Test Interactions

Methyldopa may interfere with measurement of: urinary uric acid by the phosphotungstate method, serum creatinine by the alkaline picrate method, and SGOT by colorimetric methods. Interference with spectrophotometric methods for SGOT analysis has not been reported.

Since methyldopa causes fluorescence in urine samples at the same wave lengths as catecholamines, falsely high levels of urinary catecholamines may be reported. This will interfere with the diagnosis of pheochromocytoma. It is important to recognize this phenomenon before a patient with a possible pheochromocytoma is subjected to surgery. Methyldopa does not interfere with measurement of VMA (vanillylmandelic acid), a test for pheochromocytoma, by those methods which convert VMA to vanillin. Methyldopa is not recommended for the treatment of patients with pheochromocytoma. Rarely, when urine is exposed to air after voiding, it may darken because of breakdown of methyldopa or its metabolites.

Carcinogenesis, Mutagenesis, Impairment of Fertility

No evidence of a tumorigenic effect was seen when methyldopa was given for two years to mice at doses up to 1,800 mg/kg/day or to rats at doses up to 240 mg/kg/day (30 and 4 times the maximum recommended human dose in mice and rats, respectively, when compared on the basis of body weight; 2.5 and 0.6 times the maximum recommended human dose in mice and rats, respectively, when compared on the basis of body surface area; calculations assume a patient weight of 50 kg).

Methyldopa was not mutagenic in the Ames Test and did not increase chromosomal aberration or sister chromatid exchanges in Chinese hamster ovary cells. These in vitro studies were carried out both with and without exogenous metabolic activation.

Fertility was unaffected when methyldopa was given to male and female rats at 100 mg/kg/day (1.7 times the maximum daily human dose when compared on the basis of body weight; 0.2 times the maximum daily human dose when compared on the basis of body surface area). Methyldopa decreased sperm count, sperm motility, the number of late spermatids and the male fertility index when given to male rats at 200 and 400 mg/kg/day (3.3 and 6.7 times the maximum daily human dose when compared on the basis of body weight; 0.5 and 1 times the maximum daily human dose when compared on the basis of body surface area).

Pregnancy

Pregnancy Category B. Reproduction studies performed with methyldopa at oral doses up to 1,000 mg/kg in mice, 200 mg/kg in rabbits and 100 mg/kg in rats revealed no evidence of harm to the fetus. These doses are 16.6 times, 3.3 times and 1.7 times, respectively, the maximum daily human dose when compared on the basis of body weight; 1.4 times, 1.1 times and 0.2 times, respectively, when compared on the basis of body surface area; calculations assume a patient weight of 50 kg. There are, however, no adequate and well-controlled studies in pregnant women in the first trimester of pregnancy. Because animal reproduction studies are not always predictive of human response, Methyldopa should be used during pregnancy only if clearly needed.

Published reports of the use of methyldopa during all trimesters indicate that if this drug is used during pregnancy the possibility of fetal harm appears remote. In five studies, three of which were controlled, involving 332 pregnant hypertensive women, treatment with Methyldopa was associated with an improved fetal outcome. The majority of these women were in the third trimester when methyldopa therapy was begun.

In one study, women who had begun methyldopa treatment between weeks 16 and 20 of pregnancy gave birth to infants whose average head circumference was reduced by a small amount (34.2 ± 1.7 cm vs. 34.6 ± 1.3 cm [mean ± 1 S.D.]). Long-term follow up of 195 (97.5%) of the children born to methyldopa-treated pregnant women (including those who began treatment between weeks 16 and 20) failed to uncover any significant adverse effect on the children. At four years of age, the developmental delay commonly seen in children born to hypertensive mothers was less evident in those whose mothers were treated with methyldopa during pregnancy than those whose mothers were untreated. The children of the treated group scored consistently higher than the children of the untreated group on five major indices of intellectual and motor development. At age seven and one-half developmental scores and intelligence indices showed no significant differences in children of treated or untreated hypertensive women.

Nursing Mothers

Methyldopa appears in breast milk. Therefore, caution should be exercised when methyldopa is given to a nursing woman.

Pediatric Use

There are no well-controlled clinical trials in pediatric patients. Information on dosing in pediatric patients is supported by evidence from published literature regarding the treatment of hypertension in pediatric patients. (See DOSAGE AND ADMINISTRATION)

Geriatric Use

Of the total number of subjects (1,685) in clinical studies of Methyldopa, 223 patients were 65 years of age and over while 33 patients were 75 years of age and over. No overall differences in safety or effectiveness were observed between these subjects and younger subjects, and other reported clinical experience has not identified differences in responses between the elderly and younger patients, but greater sensitivity of some older individuals cannot be ruled out. (See DOSAGE AND ADMINISTRATION)

This drug is known to be substantially excreted by the kidney, and the risk of toxic reactions to this drug may be greater in patients with impaired renal function. Because elderly patients are more likely to have decreased renal function, care should be taken in dose selection and it may be useful to monitor renal function.

ADVERSE REACTIONS

Sedation, usually transient, may occur during the initial period of therapy or whenever the dose is increased. Headache, asthenia, or weakness may be noted as early and transient symptoms. However, significant adverse effects due to Methyldopa have been infrequent and this agent usually is well tolerated.

The following adverse reactions have been reported and, within each category, are listed in order of decreasing severity.

Cardiovascular: Aggravation of angina pectoris, congestive heart failure, prolonged carotid sinus hypersensitivity, orthostatic hypotension (decrease daily dosage), edema or weight gain, bradycardia.

Digestive: Pancreatitis, colitis, vomiting, diarrhea, sialadenitis, sore or “black” tongue, nausea, constipation, distension, flatus, dryness of mouth.

Endocrine: Hyperprolactinemia.

Hematologic: Bone marrow depression, leukopenia, granulocytopenia, thrombocytopenia, hemolytic anemia; positive tests for antinuclear antibody, LE cells, and rheumatoid factor, positive Coombs test.

Hepatic: Liver disorders including hepatitis, jaundice, abnormal liver function tests (see WARNINGS).

Hypersensitivity: Myocarditis, pericarditis, vasculitis, lupus-like syndrome, drug-related fever, eosinophilia.

Nervous System/Psychiatric: Parkinsonism, Bell's palsy, decreased mental acuity, involuntary choreoathetotic movements, symptoms of cerebrovascular insufficiency, psychic disturbances including nightmares and reversible mild psychoses or depression, headache, sedation, asthenia or weakness, dizziness, lightheadedness, paresthesias.

Metabolic: Rise in BUN.

Musculoskeletal: Arthralgia, with or without joint swelling; myalgia.

Respiratory: Nasal stuffiness.

Skin: Toxic epidermal necrolysis, rash.

Urogenital: Amenorrhea, breast enlargement, gynecomastia, lactation, impotence, decreased libido.

OVERDOSAGE

Acute overdosage may produce acute hypotension with other responses attributable to brain and gastrointestinal malfunction (excessive sedation, weakness, bradycardia, dizziness, lightheadedness, constipation, distention, flatus, diarrhea, nausea, vomiting).

In the event of overdosage, symptomatic and supportive measures should be employed. When ingestion is recent, gastric lavage or emesis may reduce absorption. When ingestion has been earlier, infusions may be helpful to promote urinary excretion. Otherwise, management includes special attention to cardiac rate and output, blood volume, electrolyte balance, paralytic ileus, urinary function and cerebral activity.

Sympathomimetic drugs [e.g., levarterenol, epinephrine, ARAMINE* (Metaraminol Bitartrate)] may be indicated. Methyldopa is dialyzable.

The oral LD50 of methyldopa is greater than 1.5 g/kg in both the mouse and the rat.

DOSAGE AND ADMINISTRATION

ADULTS

Initiation of Therapy

The usual starting dosage of Methyldopa is 250 mg two or three times a day in the first 48 hours. The daily dosage then may be increased or decreased, preferably at intervals of not less than two days, until an adequate response is achieved. To minimize the sedation, start dosage increases in the evening. By adjustment of dosage, morning hypotension may be prevented without sacrificing control of afternoon blood pressure.

When methyldopa is given to patients on other antihypertensives, the dose of these agents may need to be adjusted to effect a smooth transition. When Methyldopa is given with antihypertensives other than thiazides, the initial dosage of Methyldopa should be limited to 500 mg daily in divided doses; when Methyldopa is added to a thiazide, the dosage of thiazide need not be changed.

Maintenance Therapy

The usual daily dosage of Methyldopa is 500 mg to 2 g in two to four doses. Although occasional patients have responded to higher doses, the maximum recommended daily dosage is 3 g. Once an effective dosage range is attained, a smooth blood pressure response occurs in most patients in 12 to 24 hours. Since methyldopa has a relatively short duration of action, withdrawal is followed by return of hypertension usually within 48 hours. This is not complicated by an overshoot of blood pressure.

Occasionally tolerance may occur, usually between the second and third month of therapy. Adding a diuretic or increasing the dosage of methyldopa frequently will restore effective control of blood pressure. A thiazide may be added at any time during methyldopa therapy and is recommended if therapy has not been started with a thiazide or if effective control of blood pressure cannot be maintained on 2 g of methyldopa daily.

Methyldopa is largely excreted by the kidney and patients with impaired renal function may respond to smaller doses. Syncope in older patients may be related to an increased sensitivity and advanced arteriosclerotic vascular disease. This may be avoided by lower doses. (See PRECAUTIONS, Geriatric Use)

PEDIATRIC PATIENTS

Initial dosage is based on 10 mg/kg of body weight daily in two to four doses. The daily dosage then is increased or decreased until an adequate response is achieved. The maximum dosage is 65 mg/kg or 3 g daily, whichever is less. (See PRECAUTIONS, Pediatric Use)

HOW SUPPLIED

- Methyldopa Tablets, USP , 250 mg, are White, round film coated tablets, debossed with “CE” over “87” on one side and plain on the other side. They are supplied as follows:
  NDC 62135-321-90 bottles of 90
  NDC 62135-321-18 bottles of 180
  Methyldopa Tablets, USP , 500 mg, are White, round film coated tablets, debossed with “CE” over “88” on one side and plain on the other side. They are supplied as follows:
  NDC 62135-322-90 bottles of 90
  NDC 62135-322-18 bottles of 180

Storage

Store Methyldopa Tablets at controlled room temperature 20° to 25°C (68° to 77°F) [see USP].

Manufactured for:

Chartwell RX, LLC

Congers, NY 10920

L71158

Rev. 11/2022

PACKAGE LABEL.PRINCIPAL DISPLAY PANEL

Methyldopa Tablets USP 250 mg - NDC-62135-321-90-90's Bottle Label

Methyldopa Tablets USP 250 mg - NDC 62135-321-18-180's Bottle Label

Methyldopa Tablets USP 500 mg - NDC 62135-322-90-90's Bottle Label

Methyldopa Tablets USP 500 mg - NDC 62135-322-18-180's Bottle Label